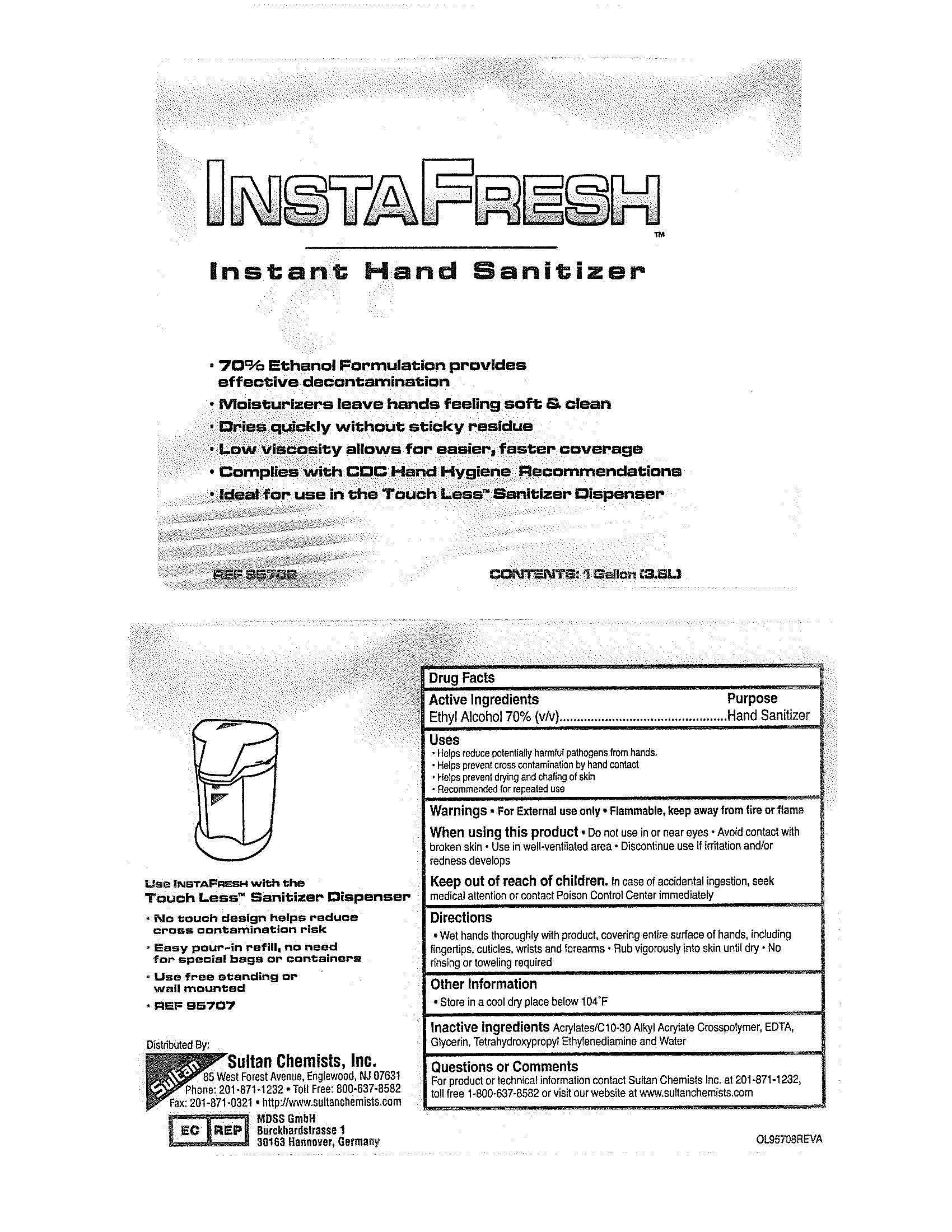 DRUG LABEL: InstaFresh
NDC: 0699-0957 | Form: LIQUID
Manufacturer: DSHealthcare
Category: otc | Type: HUMAN OTC DRUG LABEL
Date: 20110429

ACTIVE INGREDIENTS: Alcohol 70 mL/100 mL
INACTIVE INGREDIENTS: CARBOMER INTERPOLYMER TYPE A (55000 MPA.S)); EDETIC ACID; GLYCERIN; WATER; EDETOL

Drug Facts

Active Ingredients

Ethyl Alcohol 70% (v/v)

Purpose

Hand Sanitizer

Uses

Helps reduce potentially harmful pathogens from hands

Helps prevent cross contamination by hand contact

Helps prevent drying and chafing of skin

Recommended for repeated use

Warnings

For External use only

Flammable, keep away from fire or flame

When using this product

Do not use in or near the eyes

Avoid contact with broken skin

Use in well-ventilated area

Discontinue use if irritation and/or redness develops

Keep out of reach of children.

In case of accidental ingestion, seek medical attention or contact Poison Control Center immediately

Directions

Wet hands thoroughly with product, covering entire surface of hands, including fingertips, cuticles, wrists and forearms

Rub vigorously into skin until dry

No rinsing or toweling required

Other Information

Store in a cool dry place below 104 F

Inactive ingredients

Acrylates/C10-30 Alkyl Acrylate Crosspolymer, EDTA, Glycerin. Tetrahydroxypropyl Ethylenediamine and Water

Questions or Comments

For product or technical information contact Sultan Chemists Inc. at 201-871-1232, toll free 1-800-637-8582 or visit our website at www.sultanchemists.com

PACKAGE LABEL

InstaFresh

Instant Hand Sanitizer

70% Ethanol Formulation provides effective decontamination

Moisturizers leave hands feeling soft and clean

Dries quickly without sticky residue

Low viscosity allows for easier, faster coverage

Complies with CDC Hand Hygiene Recommendations

Ideal for use in the Touch Less Sanitizer Dispenser

REF 95708

CONTENTS: 1 Gallon (3.8L)